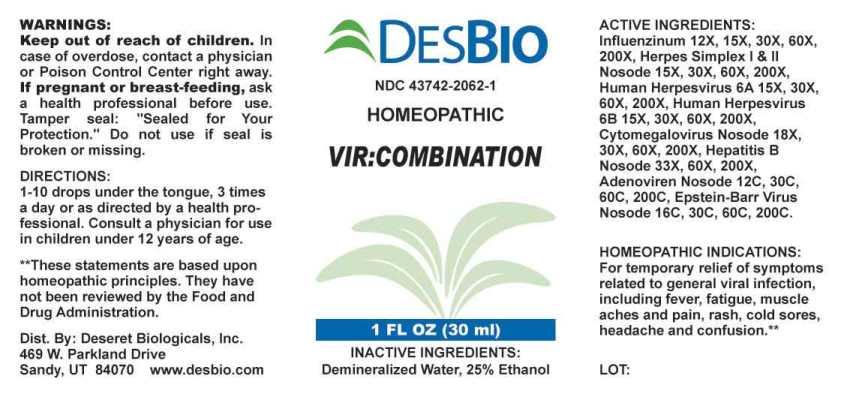 DRUG LABEL: Vir Combination
NDC: 43742-2062 | Form: LIQUID
Manufacturer: Deseret Biologicals, Inc.
Category: homeopathic | Type: HUMAN OTC DRUG LABEL
Date: 20240115

ACTIVE INGREDIENTS: INFLUENZA A VIRUS A/VICTORIA/2570/2019 IVR-215 (H1N1) ANTIGEN (UV, FORMALDEHYDE INACTIVATED) 12 [hp_X]/1 mL; INFLUENZA A VIRUS A/DARWIN/9/2021 IVR-228 (H3N2) ANTIGEN (UV, FORMALDEHYDE INACTIVATED) 12 [hp_X]/1 mL; INFLUENZA B VIRUS B/AUSTRIA/1359417/2021 BVR-26 ANTIGEN (UV, FORMALDEHYDE INACTIVATED) 12 [hp_X]/1 mL; INFLUENZA B VIRUS B/PHUKET/3073/2013 ANTIGEN (UV, FORMALDEHYDE INACTIVATED) 12 [hp_X]/1 mL; HUMAN HERPESVIRUS 1 15 [hp_X]/1 mL; HUMAN HERPESVIRUS 2 15 [hp_X]/1 mL; HUMAN HERPESVIRUS 6 15 [hp_X]/1 mL; HUMAN HERPESVIRUS 5 15 [hp_X]/1 mL; HEPATITIS B VIRUS 33 [hp_X]/1 mL; HUMAN ADENOVIRUS E SEROTYPE 4 STRAIN CL-68578 ANTIGEN 12 [hp_C]/1 mL; HUMAN ADENOVIRUS B SEROTYPE 7 STRAIN 55142 ANTIGEN 12 [hp_C]/1 mL; HUMAN HERPESVIRUS 4 16 [hp_C]/1 mL
INACTIVE INGREDIENTS: WATER; ALCOHOL

DRUG FACTS:

ACTIVE INGREDIENTS:

Influenzinum (2022-2023) 12X, 15X, 30X, 60X, 200X, Herpes Simplex 1 15X, 30X, 60X, 200X, Herpes Simplex 2 15X, 30X, 60X, 200X, Human Herpesvirus 6A 15X, 30X, 60X, 200X, Human Herpesvirus 6B 15X, 30X, 60X, 200X, Cytomegalovirus Nosode 18X, 30X, 60X, 200X, Hepatitis B Nosode 33X, 60X, 200X, Adenoviren Nosode 12C, 30C, 60C 200C, Epstein-Barr Virus Nosode 16C, 30C, 60C, 200C.

HOMEOPATHIC INDICATIONS:

For temporary relief of symptoms related to general viral infection, including fever, fatigue, muscle aches and pain, rash, cold sores, headache and confusion.**

**These statements are based upon homeopathic principles. They have not been reviewed by the Food and Drug Administration.

WARNINGS:

Keep out of reach of children. In case of overdose, contact a physician or Poison Control Center right away.

If pregnant or breast-feeding, ask a health professional before use.

Tamper seal: "Sealed for Your Protection." Do not use if seal is broken or missing.

Keep out of reach of children. In case of overdose, contact a physician or Poison Control Center right away.

DIRECTIONS:

1-10 drops under the tongue, 3 times a day or as directed by a health professional. Consult a physician for use in children under 12 years of age.

HOMEOPATHIC INDICATIONS:

For temporary relief of symptoms related to general viral infection, including fever, fatigue, muscle aches and pain, rash, cold sores, headache and confusion.**

**These statements are based upon homeopathic principles. They have not been reviewed by the Food and Drug Administration.

INACTIVE INGREDIENTS:

Demineralized Water, 25% Ethanol

QUESTIONS:

Dist. By: Deseret Biologicals, Inc.

469 W. Parkland Drive

Sandy, UT 84070 www.desbio.com

PACKAGE LABEL DISPLAY:

DESBIO

NDC 43742-2062-1

HOMEOPATHIC

VIR:COMBINATION

1 FL OZ (30 ml)